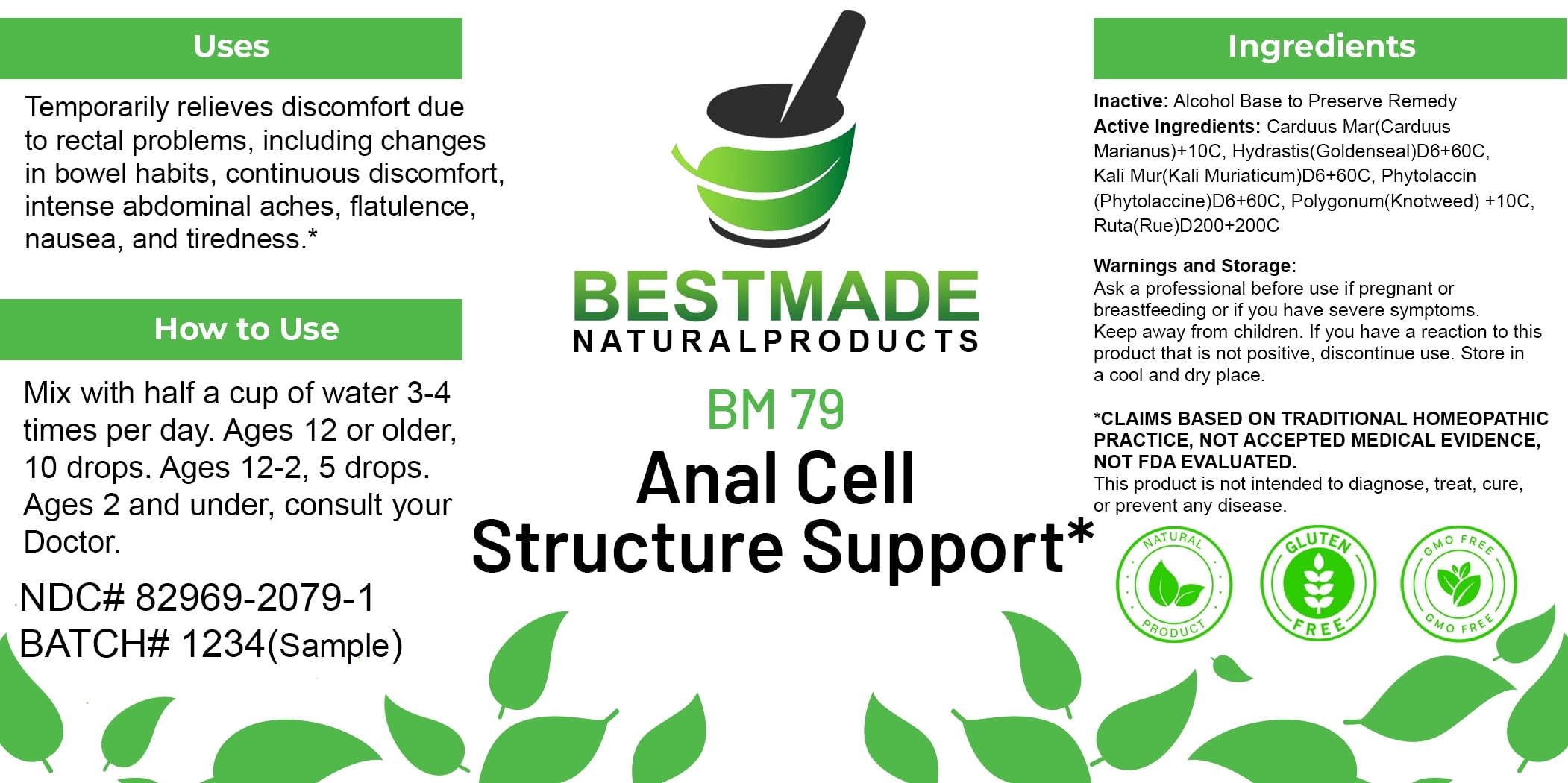 DRUG LABEL: Bestmade Natural Products BM79
NDC: 82969-2079 | Form: LIQUID
Manufacturer: Bestmade Natural Products
Category: homeopathic | Type: HUMAN OTC DRUG LABEL
Date: 20250130

ACTIVE INGREDIENTS: GOLDENSEAL 30 [hp_C]/30 [hp_C]; PERSICARIA PUNCTATA 30 [hp_C]/30 [hp_C]; PHYTOLACCA AMERICANA ROOT 30 [hp_C]/30 [hp_C]; RUTA GRAVEOLENS FLOWERING TOP 30 [hp_C]/30 [hp_C]; MILK THISTLE 30 [hp_C]/30 [hp_C]; POTASSIUM CHLORIDE 30 [hp_C]/30 [hp_C]
INACTIVE INGREDIENTS: ALCOHOL 30 [hp_C]/30 [hp_C]

BM79

DOSAGE AND ADMINISTRATION

How to Use

Mix with half a cup of water 3-4 times per day. Ages 12 or older, 10 drops. Ages 12-2, 5 drops. Ages 2 and under, consult your Doctor.

INACTIVE INGREDIENT

Ingredients

Inactive: Alcohol Base to Preserve Remedy

ACTIVE INGREDIENT

Active Ingredients: Carduus Mar (Carduus Marianus) + 10C, Hydrastis (Goldenseal) D6 + 60C, Kali Mur (Kali Muriaticum) D6 + 60C, Phytolaccin (Phytolaccine) D6 + 60C, Polygonum (Knotweed) + 10C, Ruta (Rue) D200 + 200C

Uses

Temporarily relieves discomfort due to rectal problems, including changes in bowel habits, continuous discomfort, intense abdominal aches, flatulence, nausea, and tiredness.*

*CLAIMS BASED ON TRADITIONAL HOMEOPATHIC PRACTICE, NOT ACCEPTED MEDICAL EVIDENCE, NOT FDA EVALUATED.

This product is not intended to diagnose, treat, cure, or prevent any disease.

Uses

Temporarily relieves discomfort due to rectal problems, including changes in bowel habits, continuous discomfort, intense abdominal aches, flatulence, nausea, and tiredness.*

*CLAIMS BASED ON TRADITIONAL HOMEOPATHIC PRACTICE, NOT ACCEPTED MEDICAL EVIDENCE, NOT FDA EVALUATED.

This product is not intended to diagnose, treat, cure, or prevent any disease.

KEEP OUT OF REACH OF CHILDREN

Warnings and Storage:

Ask a professional before use if pregnant or breastfeeding or if you have severe symptoms. Keep away from children. If you have a reaction to this product that is not positive, discontinue use. Store in a cool and dry place.

Warnings and Storage:

Ask a professional before use if pregnant or breastfeeding or if you have severe symptoms. Keep away from children. If you have a reaction to this product that is not positive, discontinue use. Store in a cool and dry place.

*CLAIMS BASED ON TRADITIONAL HOMEOPATHIC PRACTICE, NOT ACCEPTED MEDICAL EVIDENCE, NOT FDA EVALUATED.

This product is not intended to diagnose, treat, cure, or prevent any disease.

Entire package label